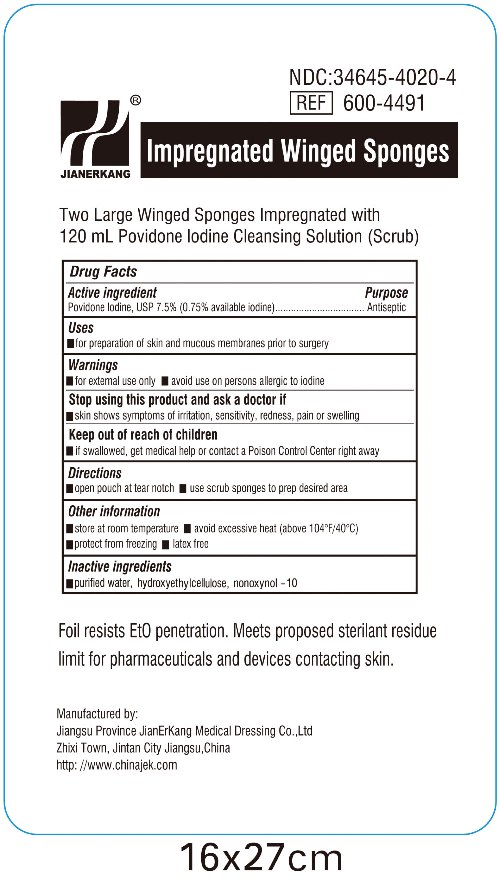 DRUG LABEL: Povidone Iodine Impregnated
NDC: 34645-4020 | Form: SPONGE
Manufacturer: Jianerkang Medical Co., Ltd
Category: otc | Type: HUMAN OTC DRUG LABEL
Date: 20231023

ACTIVE INGREDIENTS: POVIDONE-IODINE 7.5 mg/1 mL
INACTIVE INGREDIENTS: WATER; NONOXYNOL-10

Drug Facts

Active Ingredients

Povidone Iodine, USP 7.5% (0.75% available Iodine)

Purpose

Antiseptic

Uses

For preparation of skin and mucous membranes prior to surgery

Warnings

For external use only

Avoid use on persons allergic to iodine

Stop use and ask a doctor if

Skin shows symptoms of irritation, sensitivity, redness, pain or swelling

Keep out of reach of children

If swallowed, get medical help or contact Poison Control Center right away

Directions

open pouch at tear notch

use sponge sticks to prep desired area

Other information

store at room temperature avoid excessive heat (above 104oF/40oC) protect from freezing latex free

Inactive Ingredients

hydroxyethylcellulose, nonoxynol - 10, purified water